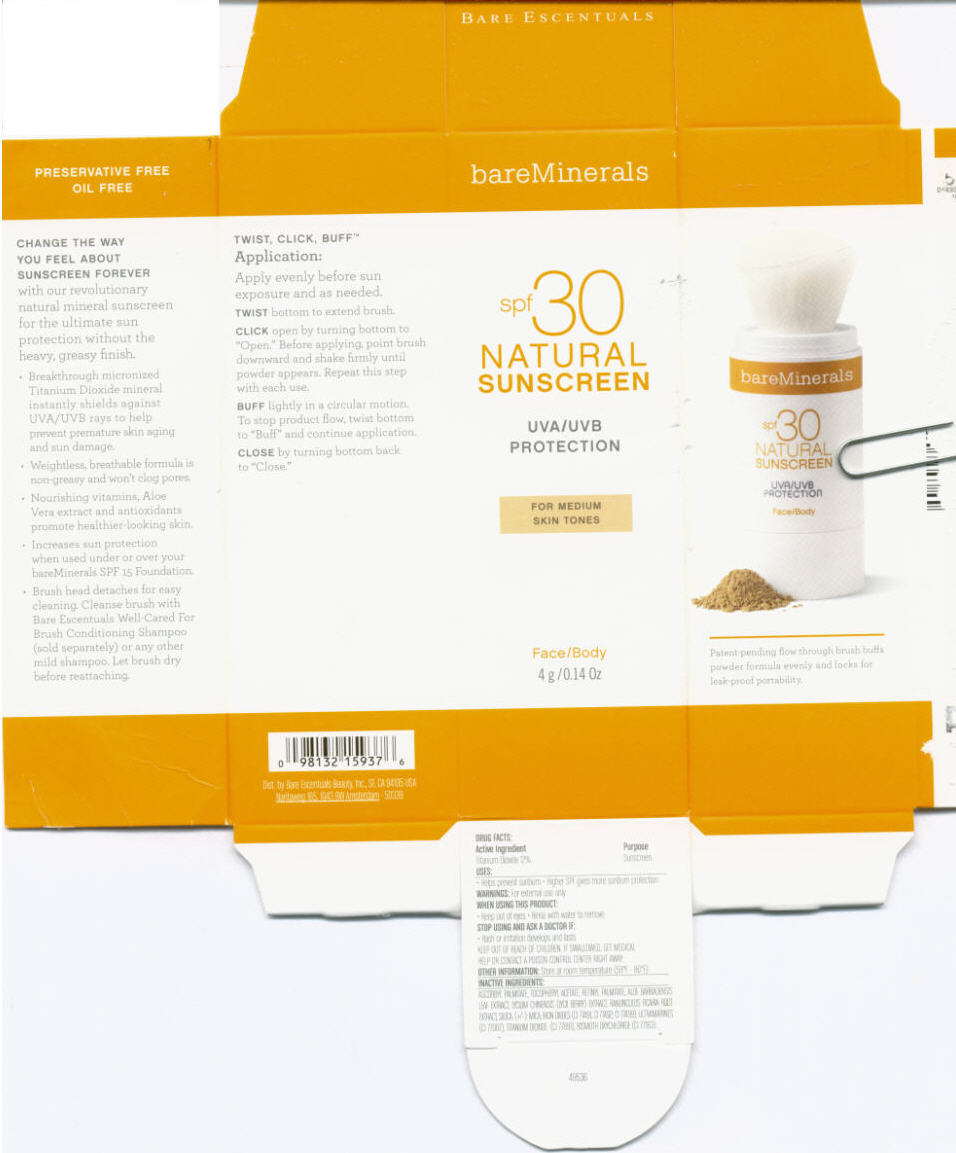 DRUG LABEL: BareMinerals 
NDC: 98132-123 | Form: POWDER
Manufacturer: Bare Escentuals Beauty Inc.
Category: otc | Type: HUMAN OTC DRUG LABEL
Date: 20110906

ACTIVE INGREDIENTS: Titanium Dioxide 12 g/100 g
INACTIVE INGREDIENTS: Ascorbyl Palmitate; Tocopherol; Vitamin A Palmitate; Aloe; Lycium Chinense Root Bark; Ranunculus Ficaria; Mica; Ferric Oxide Red; Bismuth Oxychloride

Natural Sunscreen Medium

Drug Facts

Uses

Helps prevent sunburn. Higher SPF gives more sunburn protection.

Active Ingredients

Titanium Dioxide 12%

Purpose

Sunscreen

Warnings

For external use only

When using this product

Keep out of Eyes ; Rinse with water to remove

Stop use and ask a doctor if

Rash or irritation develops or lasts.

Keep out of reach of children. If swallowed, get medical help or contact a Poison Control Center right away.

Directions

Apply evenly before sun exposure as needed.

Other information: Store at room temperature (59° to 86° F)

Inactive Ingredients

ASCORBY PALMITATE, TOCOPHERYL ACETATE, RETINYL PALMITATE, ALOE BARBADENIS LEAF EXTRACT, LYCIUM CHINESIS (LYCII BERRY) EXTRACT, RANUNCULLUS FICARIA ROOT EXTRACT, SILICA, (+/-) Mica, IRON OXIDES (CI77491, CI 77499), ULTRAMARINES (CI77007), TITANIUM DIOXIDE (CI 77891), BISMUTH OXYCLORIDE (CI 77163)

Distr. By Bare Escentuals Beauty Inc., San Francisco CA 94104 USA

PRINCIPAL DISPLAY PANEL - 4 g Jar Carton

bareMinerals

spf30
NATURAL
SUNSCREEN

UVA/UVB
PROTECTION

FOR MEDIUM
SKIN TONES

Face/Body
4 g/0.14 Oz